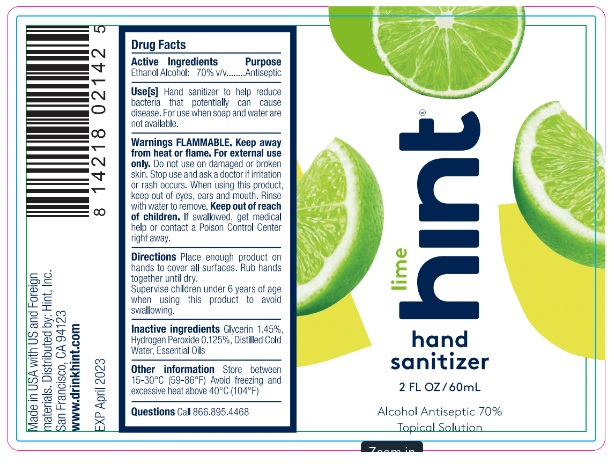 DRUG LABEL: Lime Hint Hand Sanitizer
NDC: 81915-103 | Form: SOLUTION
Manufacturer: Hint, Inc.
Category: otc | Type: HUMAN OTC DRUG LABEL
Date: 20210525

ACTIVE INGREDIENTS: ALCOHOL 70 mL/100 mL
INACTIVE INGREDIENTS: GLYCERIN; HYDROGEN PEROXIDE; WATER; LIME OIL, COLD PRESSED

lime hint® hand sanitizer

Active Ingredients

Ethanol: 70% v/v

Purpose

Antiseptic

Use[s]

Hand sanitizer to help reduce bacteria that potentially can cause disease. For use when soap and water are not available.

Warnings

FLAMMABLE. Keep away from heat or flame. For external use only. Do not use on damaged or broken skin. Stop use and ask a doctor if irritation or rash occurs. When using this product, keep out of eyes, ears and mouth. Rinse with water to remove.

Keep out of reach of children. If swallowed, get medical help or contact a Poison Control Center right away.

Directions

Place enough product on hands to cover all surfaces. Rub hands together until dry.
Supervise children under 6 years of age when using this product to avoid swallowing.

Inactive ingredients

Glycerin 1.45%, Hydrogen Peroxide 0.125%, Distilled Cold Water, Essential Oils

Other information

Store between 15-30°C (59-86°F) Avoid freezing and excessive heat above 40°C (104°F)

Questions

Call 866.895.4468

Alcohol Antiseptic 70%

Topical Solution

Made in USA with US and Foreign materials.
Distributed by: Hint, Inc.
San Francisco, CA 94123

www.drinkhint.com